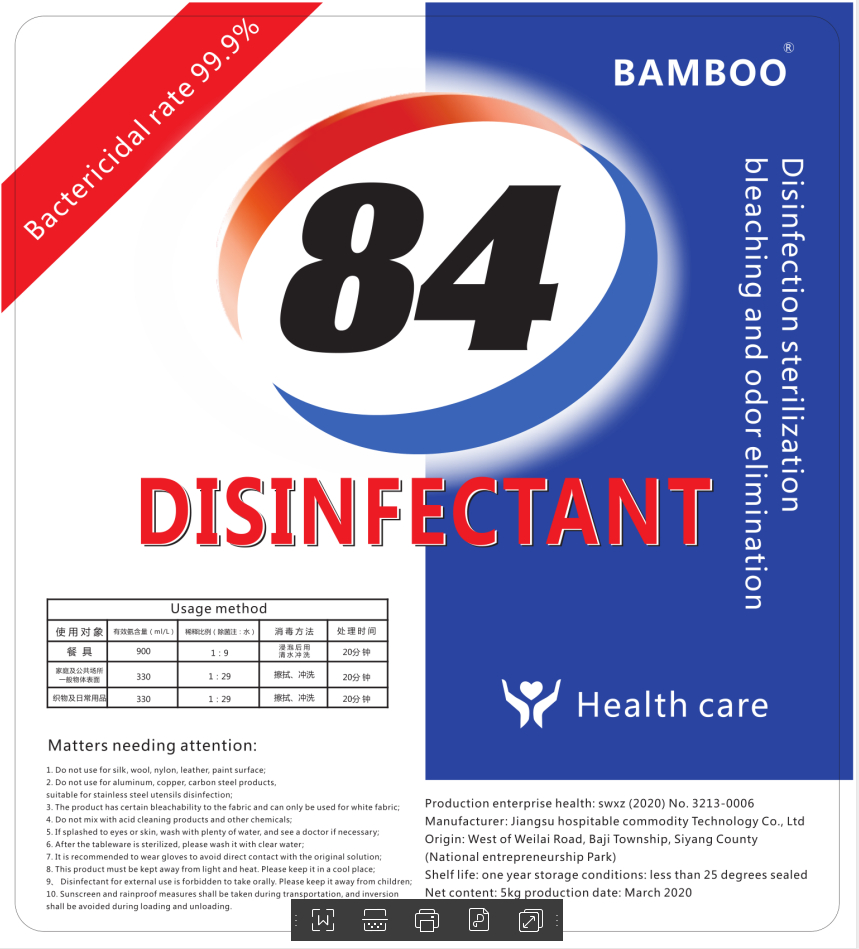 DRUG LABEL: 84 DISINFECTANT
NDC: 41254-001 | Form: LIQUID
Manufacturer: Jiangsu Hawer Amenities Technology Co.,Ltd
Category: otc | Type: HUMAN OTC DRUG LABEL
Date: 20200413

ACTIVE INGREDIENTS: SODIUM HYPOCHLORITE 25.9 g/518 g
INACTIVE INGREDIENTS: WATER

PURPOSE

Disinfection
Sterilization
No Rinseing

ACTIVE INGREDIENT

Sodium hypochlorite

Do not use for silk, wool, nylon, leather, paint surface;
Do not use for aluminum, copper, carbon steel products, suitable for stainless steel utensils disinfection;

keep out reach of children

INDICATIONS AND USAGE

The product has certain bleachability to the fabric and can only be used for white fabric;

Do not mix with acid cleaning products and other chemicals;

If splashed to eyes or skin, wash with plenty of water, and see a doctor if necessary;
After the tableware is sterilized, please wash it with clear water;

INACTIVE INGREDIENT

water

DOSAGE AND ADMINISTRATION

This product must be kept away from light and heat. Please keep it in a cool place;